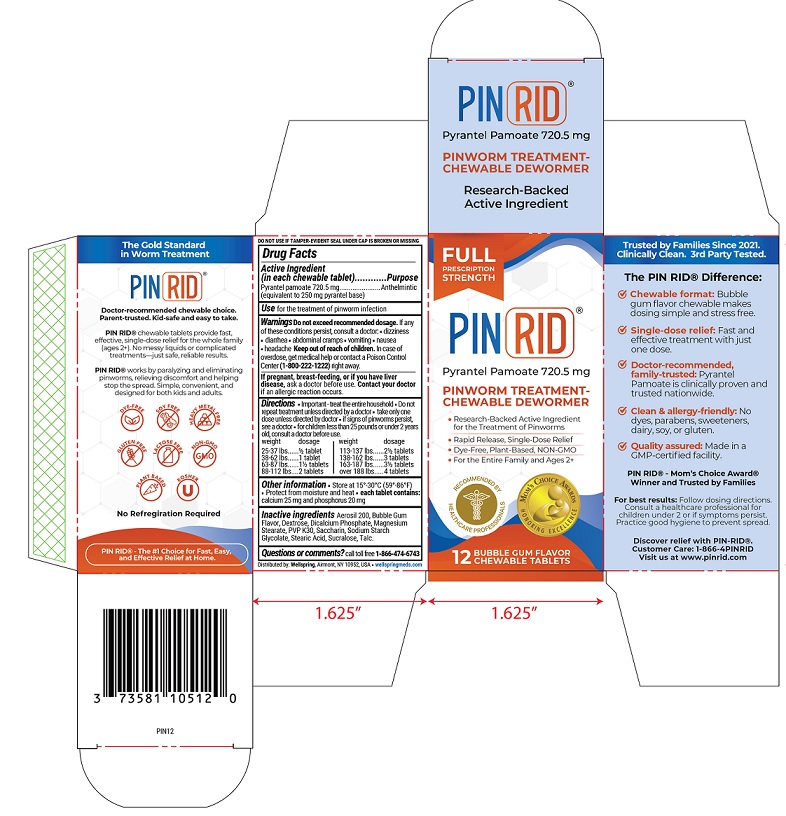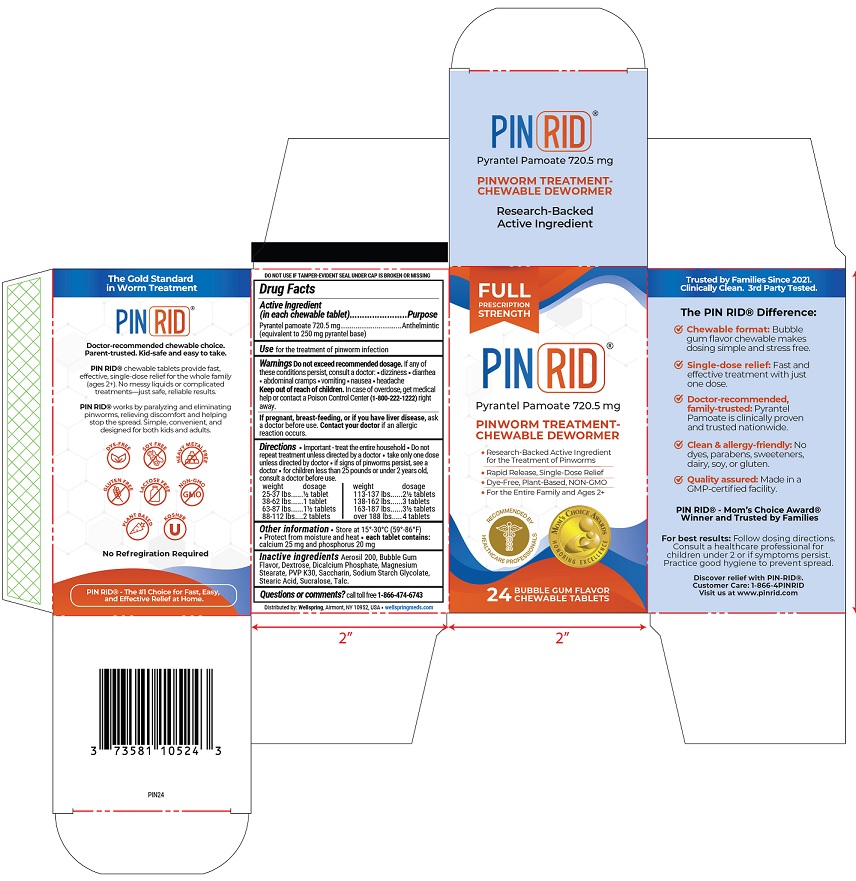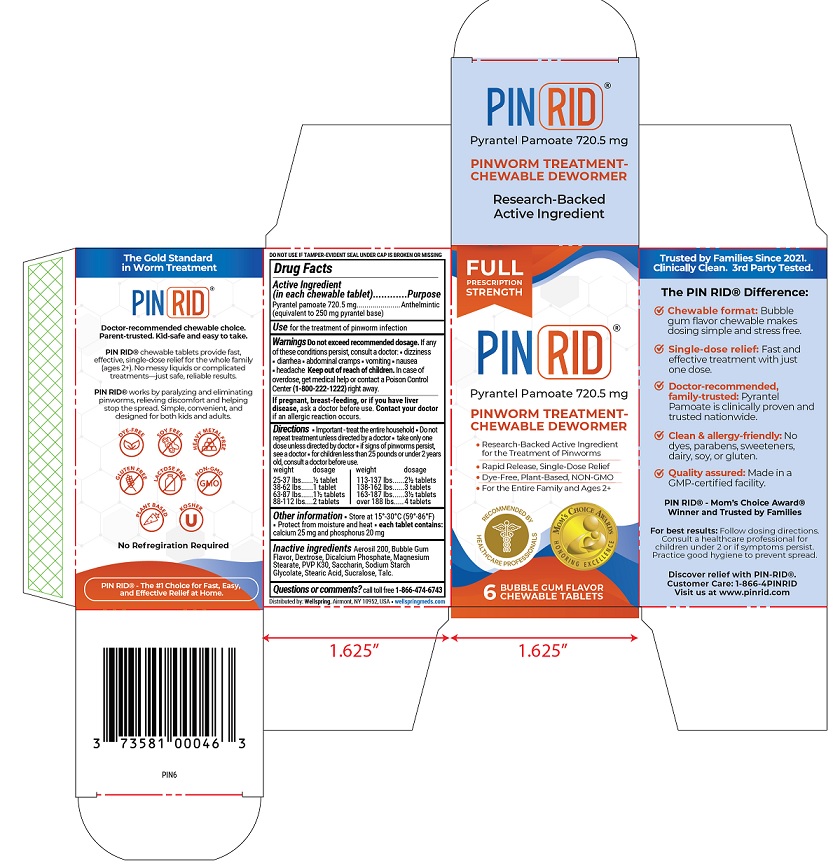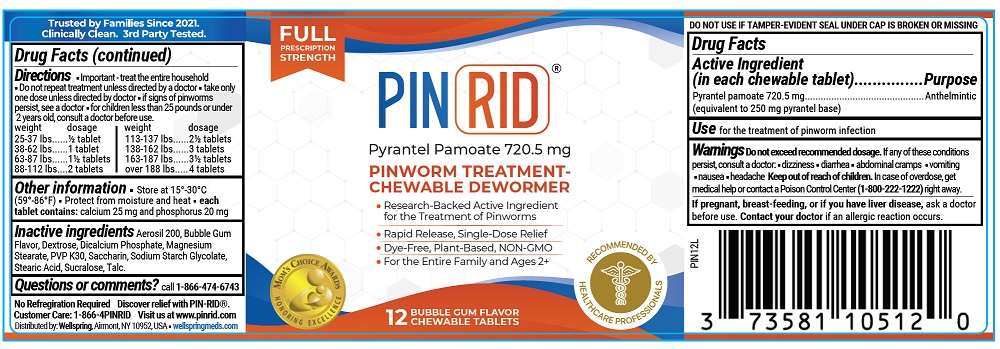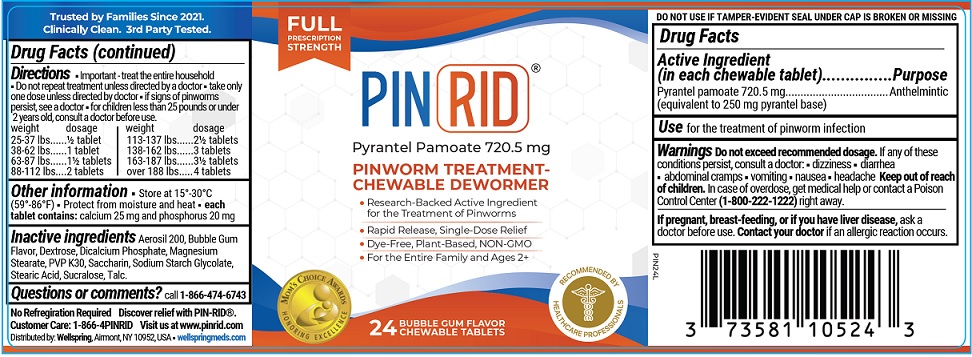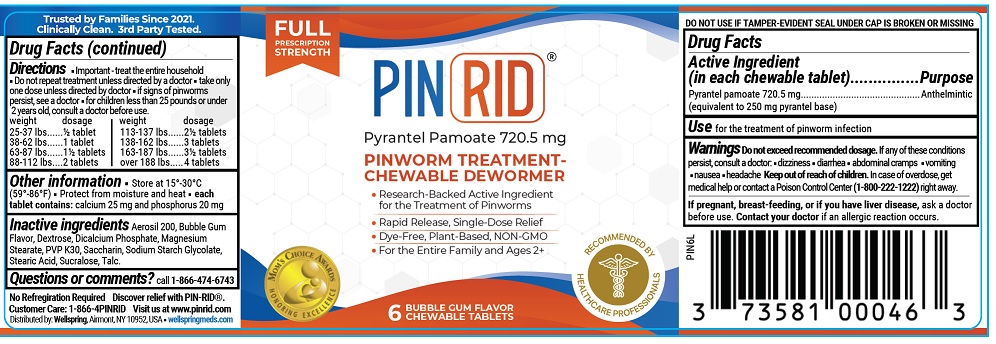 DRUG LABEL: PINRID
NDC: 73581-113 | Form: TABLET
Manufacturer: YYBA CORP
Category: otc | Type: HUMAN OTC DRUG LABEL
Date: 20260114

ACTIVE INGREDIENTS: PYRANTEL PAMOATE 250 mg/1 1
INACTIVE INGREDIENTS: POVIDONE K30; SACCHARIN; SODIUM STARCH GLYCOLATE TYPE A; STEARIC ACID; SUCRALOSE; TALC; SILICON DIOXIDE; DEXTROSE; ANHYDROUS DIBASIC CALCIUM PHOSPHATE; MAGNESIUM STEARATE

PINRID

Drug Facts

Active Ingredient (in each chewable tablet)

Pyrantel pamoate 720.5 mg

(equivalent to 250 mg pyrantel base)

Purpose

Anthelmintic

Use

for the treatment of pinworm infection

Warnings Do not exceed recommended dosage.If any of these conditions persist, consult a doctor• dizziness • diarhea • abdominal cramps • vomiting • nausea • headache

Keep out of reach of children.

In case of overdose, get medical help or contact a poison control center (1-800-222-1222) right away.

If pregnant, breast-feeding, or if you have liver disease,

ask a doctor before use. Contact your doctor if an allergic reaction occurs.

Directions

- Important- treat the entire household
- do not repeat treatment unless directed by a doctor
- take only one dose unless directed by doctor
- if signs of pinworms persist, see a doctor
- for children less than 25 pounds or under 2 years old, consult a doctor before use.

Weight | Dosage
25-37 lb | ½ tablet
38-62 lbs | 1 tablets
63-87 lbs | 1½ tablets
88-112 lbs | 2 tablets
113-137 lbs | 2½ tablets
138-162 lbs | 3 tablets
163-187 lbs | 3½ tablets
over 188 lbs | 4 tablets

Other information:

- Store at 15°-30°C (59° - 86 °F)
- Protect from moisture and heat
- each tablet contains:calcium 25 mg and phosphorus 20 mg

Intactive ingredients

Aerosil 200, Bubble Gum Flavor, Dextrose, Dicalcium Phosphate, Magnesium Stearate, PVP K30, Saccharine, Sodium Starch Glycolate, Steric Acid, Sucralose, Talc.

Questions or comments?

call toll free 1-866-474-6743